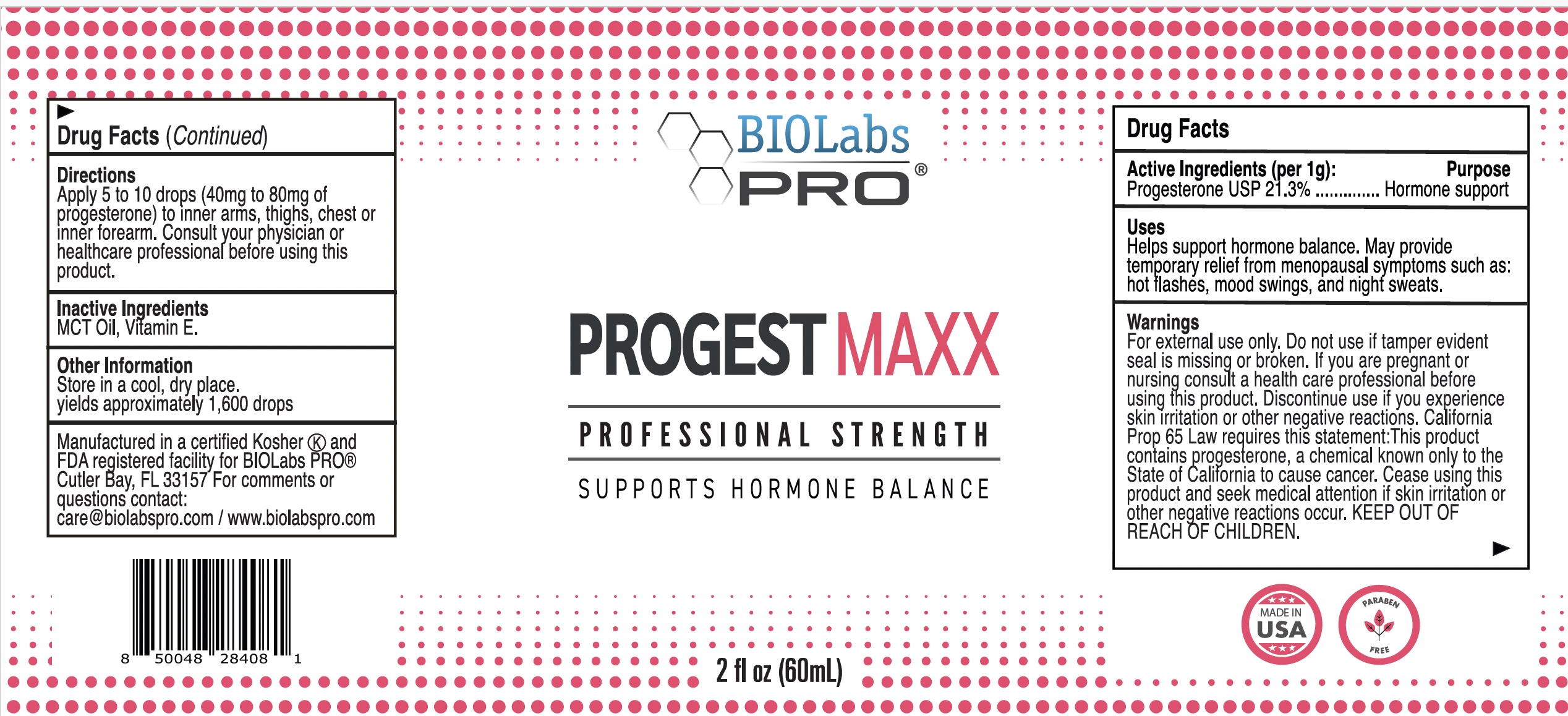 DRUG LABEL: Progest-Oil-2oz-SB
NDC: 82018-0027 | Form: OIL
Manufacturer: Shyne Brands/BIOLabs PRO
Category: otc | Type: HUMAN OTC DRUG LABEL
Date: 20250601

ACTIVE INGREDIENTS: PROGESTERONE 12.8 g/60 g
INACTIVE INGREDIENTS: VITAMIN E POLYETHYLENE GLYCOL SUCCINATE 20 g/60 g; MEDIUM-CHAIN TRIGLYCERIDES 20 g/60 g

2oz Progesterone Oil

Active Ingredient (per 1g)

Progesterone USP 21.3% .......... Hormone Support

PURPOSE

Helps support hormone balance.

INDICATIONS AND USAGE

May provide temporary relief from menopausal symptoms such as hot flashes, mood swings and night sweats.

WARNINGS

For external cosmetic use only. If pregnant or nursing, consult a healthcare professional before using this product. Cease using this product and seek medical attention if skin irritation or other negative reactions occur. Do not use if tamper-evident seal is broken or missing. California Prop 65 Law requires this statement:
This product contains progesterone, a chemical known only to the state of California to cause cancer.
KEEP OUT OF REACH OF CHILDREN.

PREGNANCY OR BREAST FEEDING

If pregnant or nursing, consult a healthcare professional before using this product.

KEEP OUT OF REACH OF CHILDREN.

DOSAGE AND ADMINISTRATION

Apply 5-10 drops (40-80mg progesterone) to inner arms, thighs, chest or apply to inner forearm and rub arms together or use as directed by your Physician.

INACTIVE INGREDIENT

MCT Oil, Vitamin E

Questions?
care@biolabspro.com
www.biolabspro.com